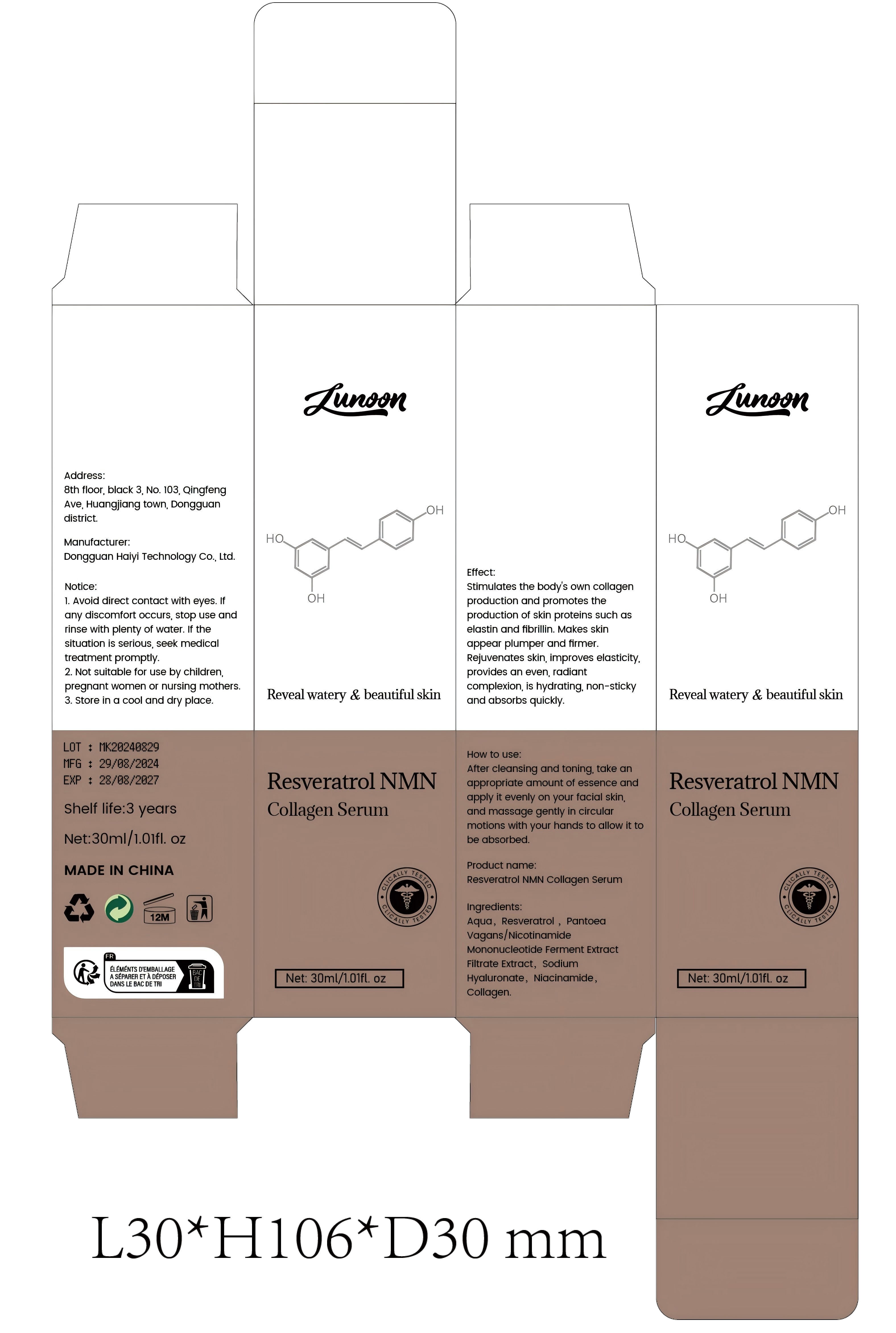 DRUG LABEL: Resveratrol NMN Collagen Serum
NDC: 84732-042 | Form: LIQUID
Manufacturer: Dongguan Haiyi Technology Co.,Ltd.
Category: otc | Type: HUMAN OTC DRUG LABEL
Date: 20241013

ACTIVE INGREDIENTS: RESVERATROL 1 mg/100 mL
INACTIVE INGREDIENTS: NIACINAMIDE; METHYL CARBOXYMETHYLPHENYL AMINOCARBOXYPROPYLPHOSPHONATE; HYALURONATE SODIUM; WATER

Active ingredient

Resveratrol

Inactive ingredient

Aqua,,Pantoea Vagans/Nicotinamide Mononucleotide Ferment Extract Filtrate Extract, sodium Hyaluronate, Niacinamide.Collagen.

Purpose section

stimulates the body's own collagen production and promotes the production of skin proteins such as elastin and fibrillin. Makes skin appear plumper and firmer.Rejuvenates skin, improves elasticity.provides an even, radiant complexion, is hydrating, non-sticky and absorbs quickly.

Warning

1. Avoid direct contact with eyes. lfany discomfort occurs, stop use andrinse with plenty of water. lf thesituation is serious, seek medicaltreatment promptly.

2. Not suitable for use by children,pregnant women or nursing mothers

3. Store in a cool and dry place.

stop use

This product may cause allergic reactions in asmall number of people.
lf you experience any discomfort,please stop using it immediately.

not use

Not suitable for use by children, pregnantor breast feeding people.

OUT OF CHILDREN

KEEP THE PRODUCT OUT OF REACH OF CHILDREN to

HOW TO USE

After cleansing and toning, take an appropriate amount of essence and apply it evenly on your facial skin,and massage gently in circularmotions with your hands to allow it tobe absorbed.

Dosage

take an appropriateamount,Use 2-3 times a week